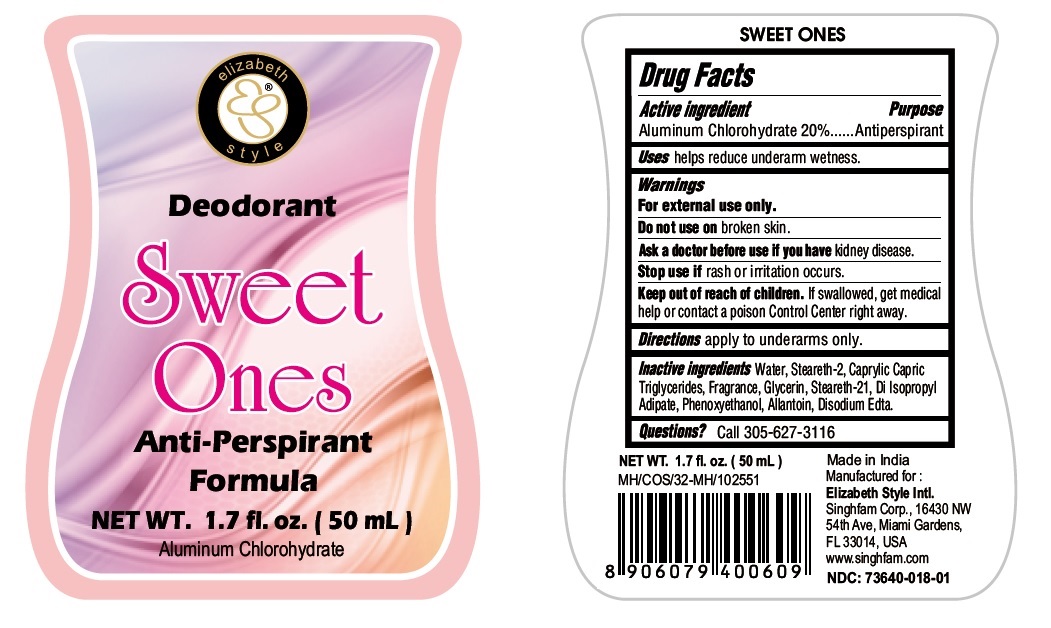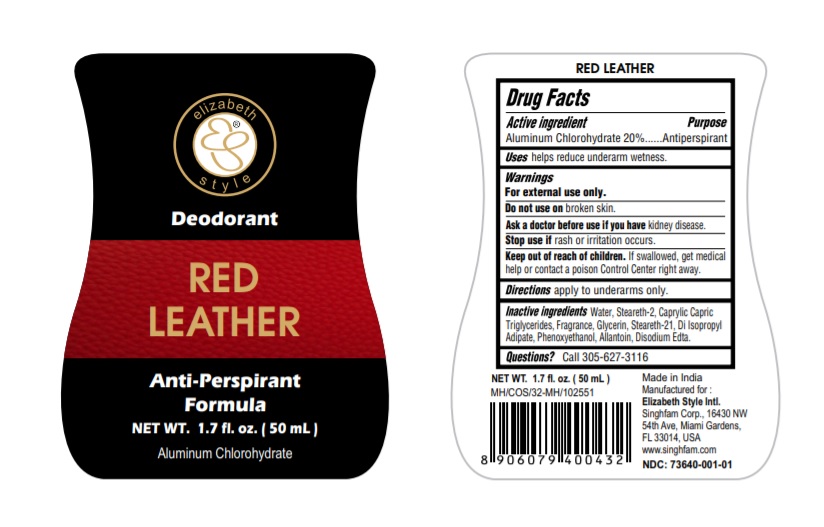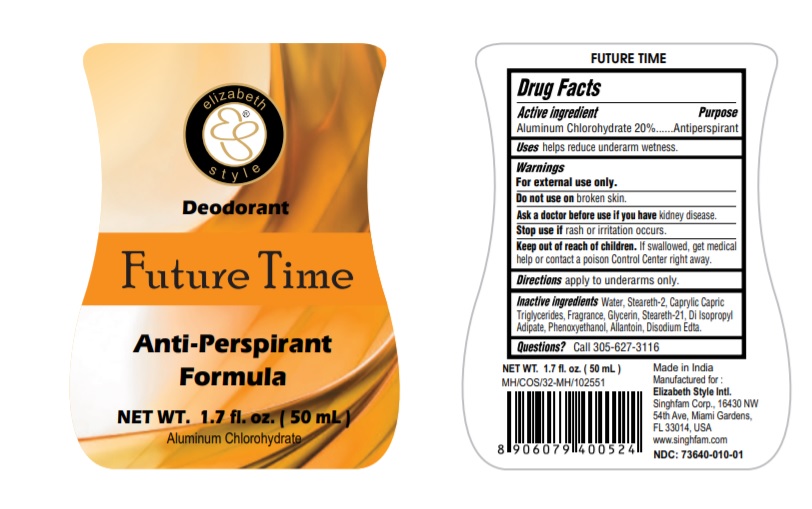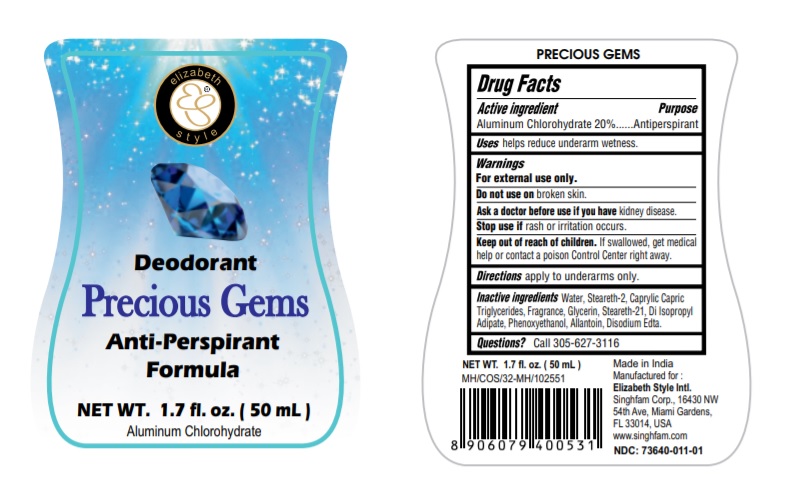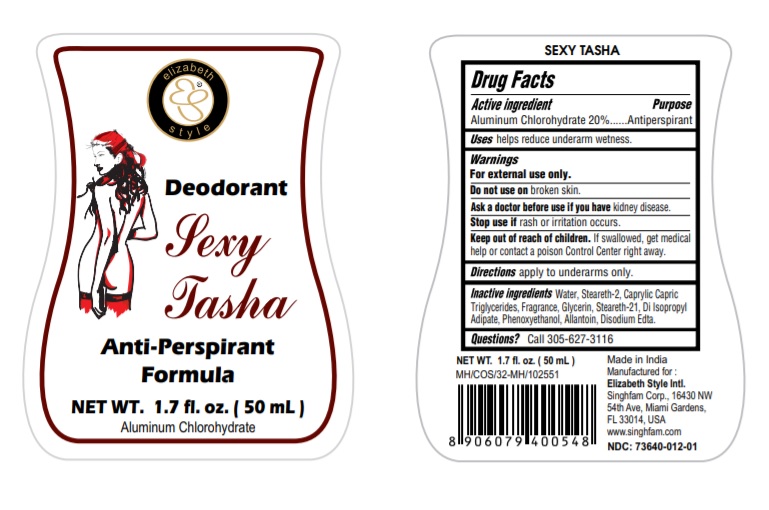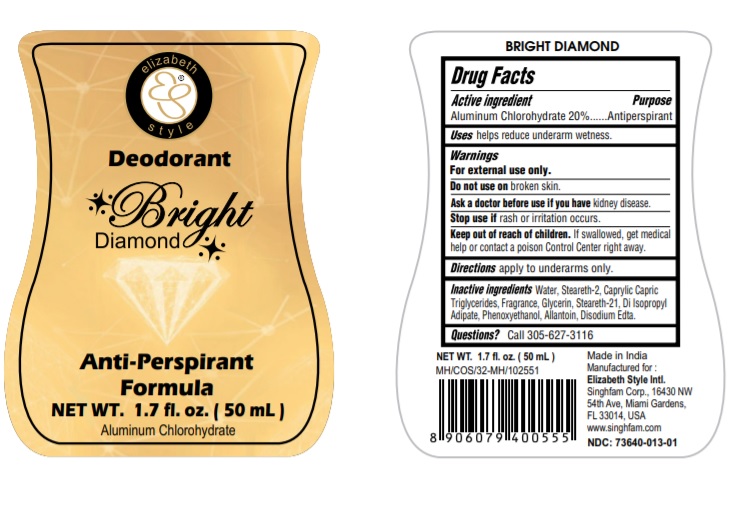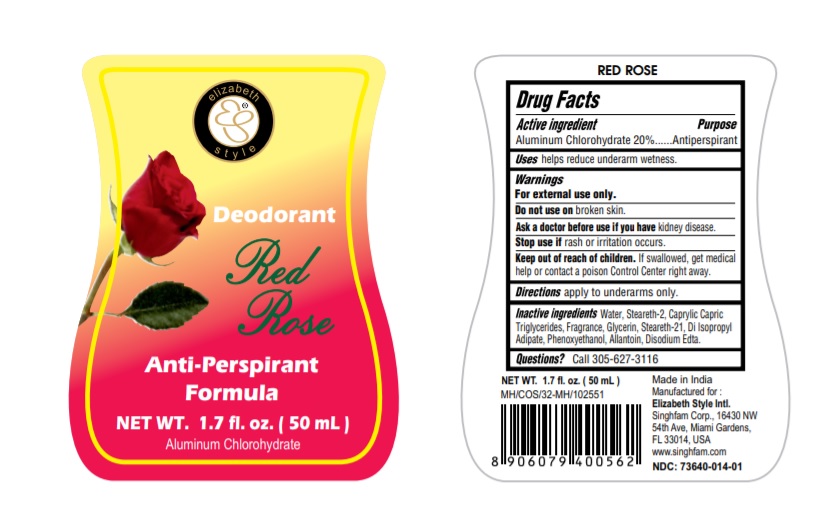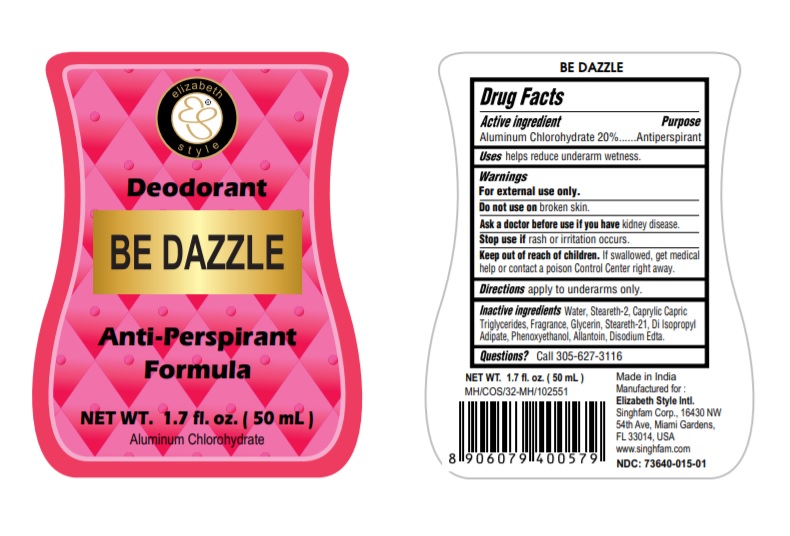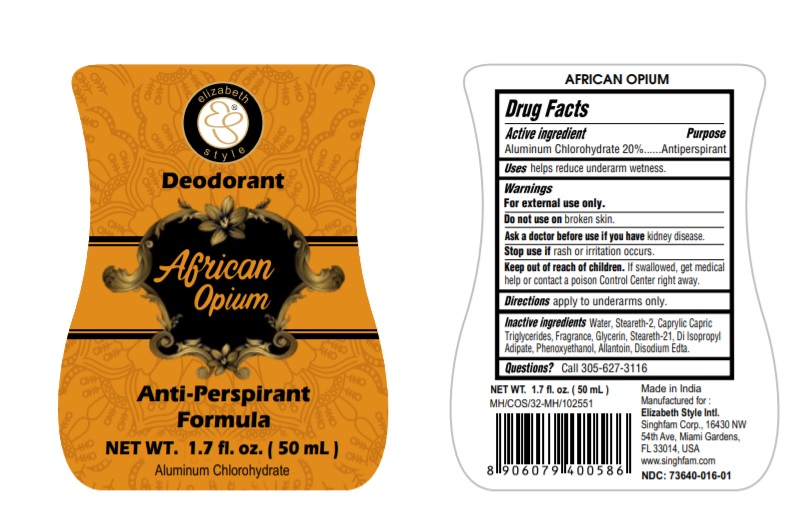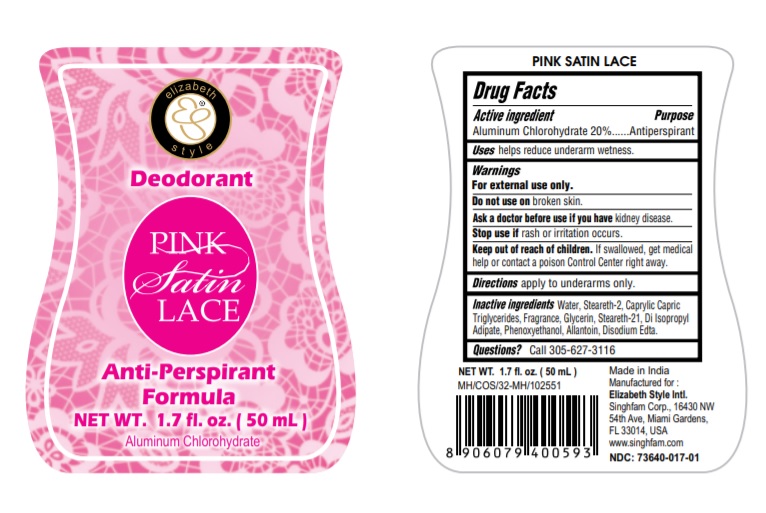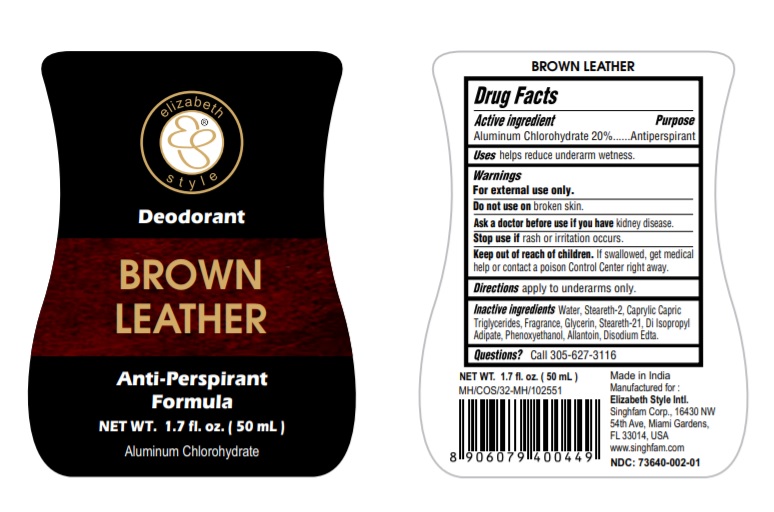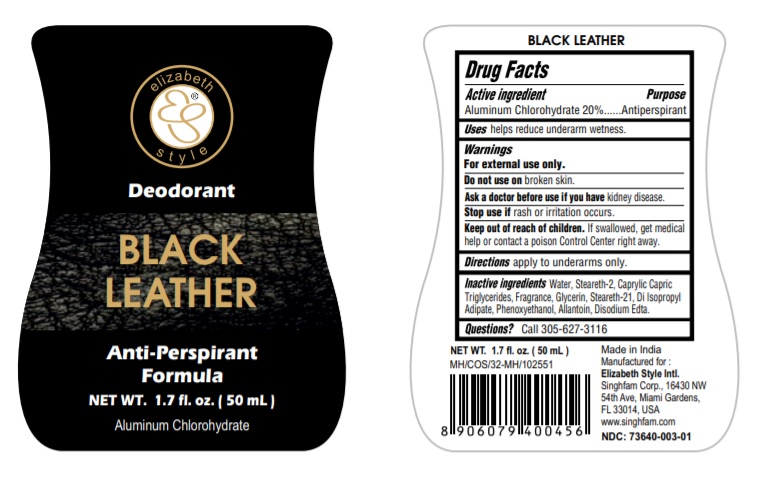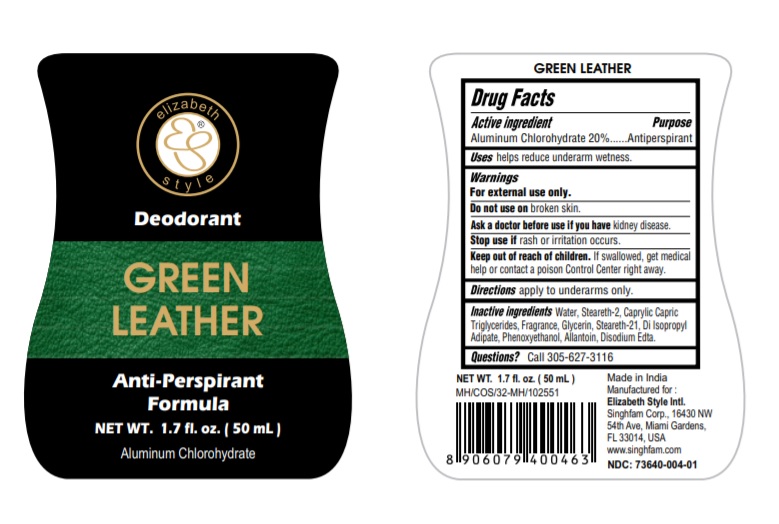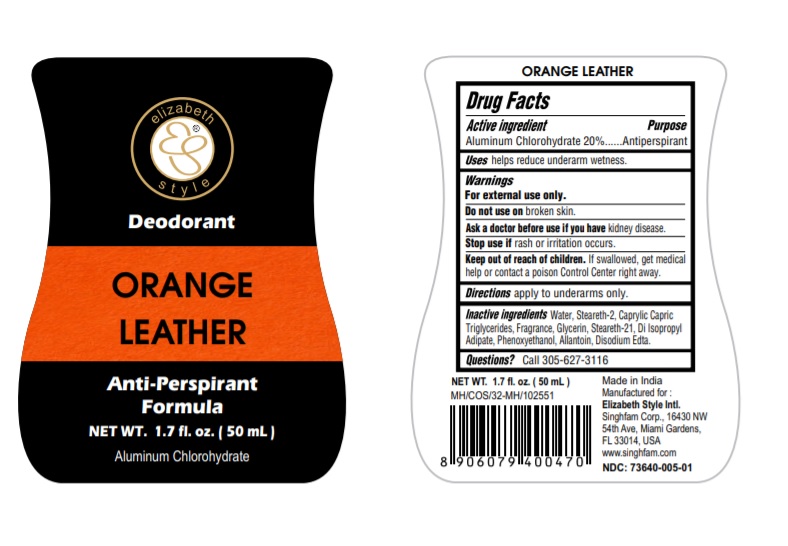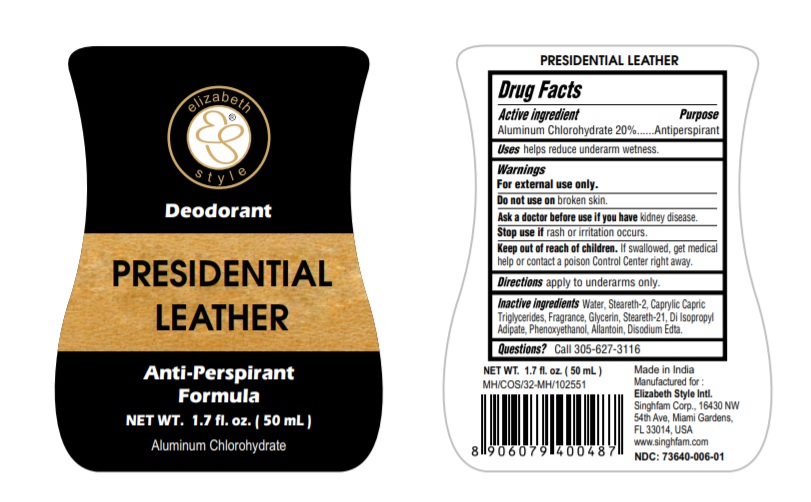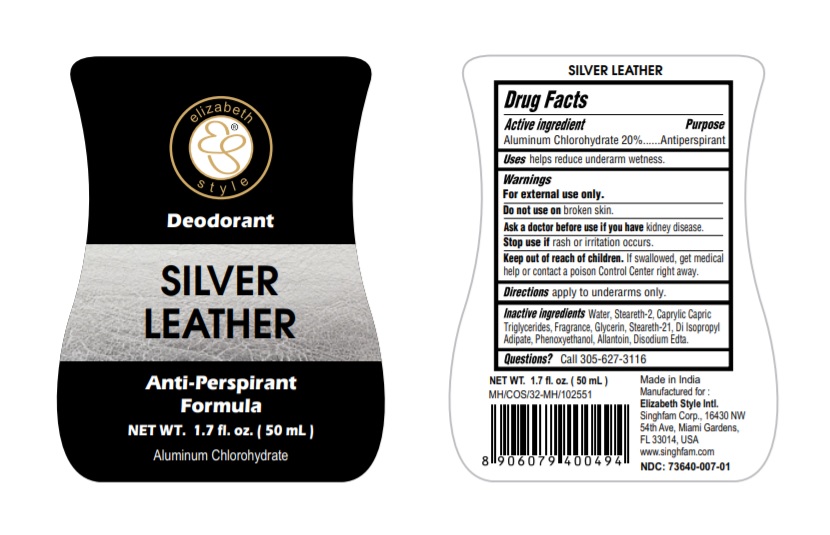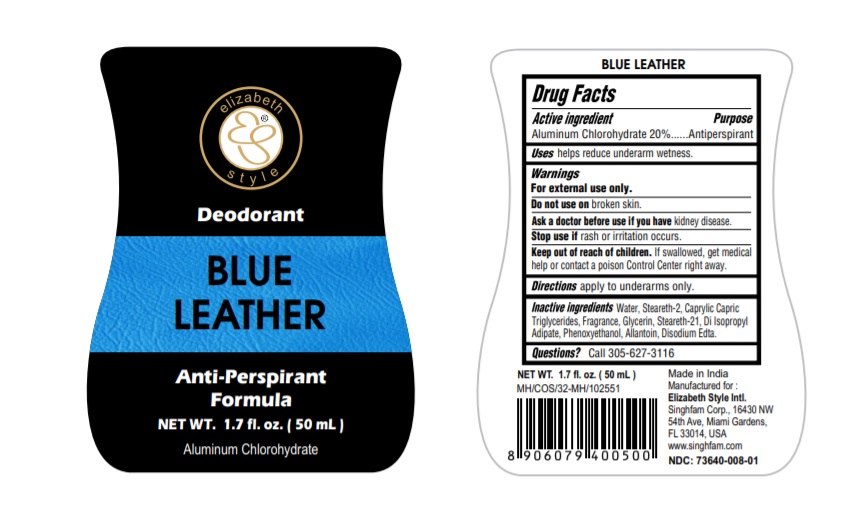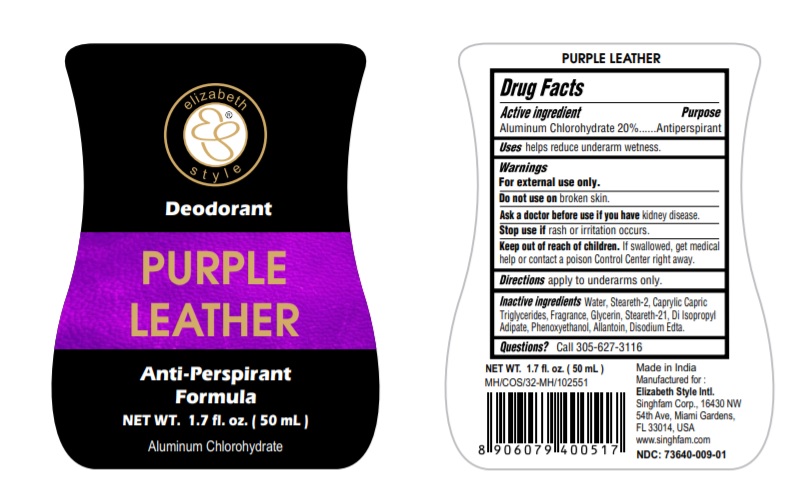 DRUG LABEL: BLACK LEATHER
NDC: 73640-003 | Form: LIQUID
Manufacturer: N. N. IMPEX
Category: otc | Type: HUMAN OTC DRUG LABEL
Date: 20210506

ACTIVE INGREDIENTS: ALUMINUM CHLOROHYDRATE 200 mg/1 mL
INACTIVE INGREDIENTS: STEARETH-2; STEARETH-21; MEDIUM-CHAIN TRIGLYCERIDES; DIISOPROPYL ADIPATE; EDETATE DISODIUM; GLYCERIN; ALLANTOIN; PHENOXYETHANOL; WATER

BLACK LEATHER
Anti-Perspirant
Deodorant

Active ingredients

Aluminum Chlorohydrate 20%

Purpose

Antiperspirant

Warnings

Warnings For external use only.

Do not use on broken skin.

Ask a doctor before use if you have kidney disease.

Stop use if rash or irritation occurs

Keep out of reach of children.

If swallowed, get medical help or contact a poison Control Center right away

Use

helps reduce underarm wetness

Directions

apply to underarms only.

Questions? Call 305-627-3116

Inactive Ingredients

Water,Steareth-2, Caprylic Capric
Triglycerides, Fragrance, Glycerin, Steareth-21, Di Isopropyl
Adipate, Phenoxyethanol, Allantoin, Disodium Edta